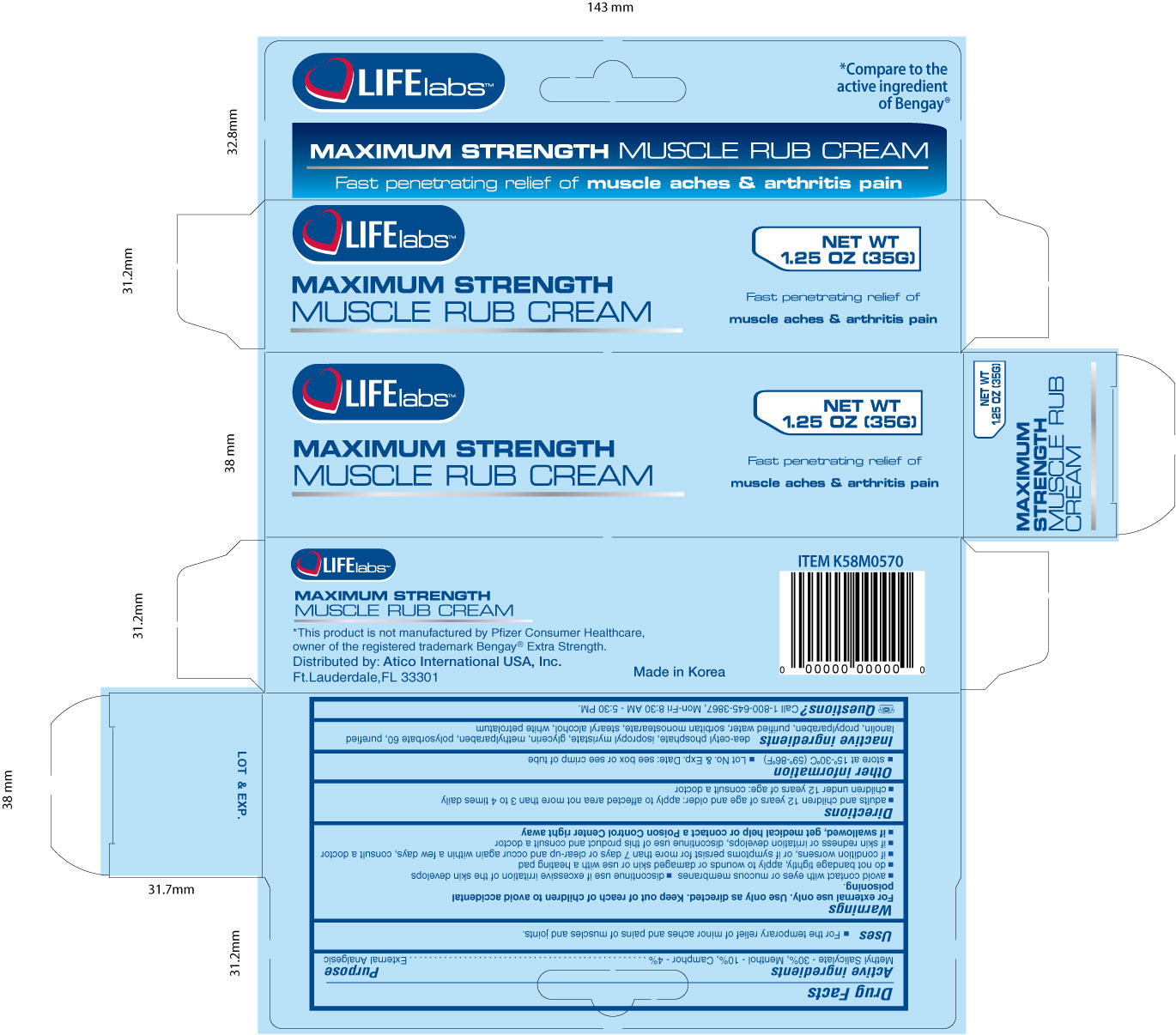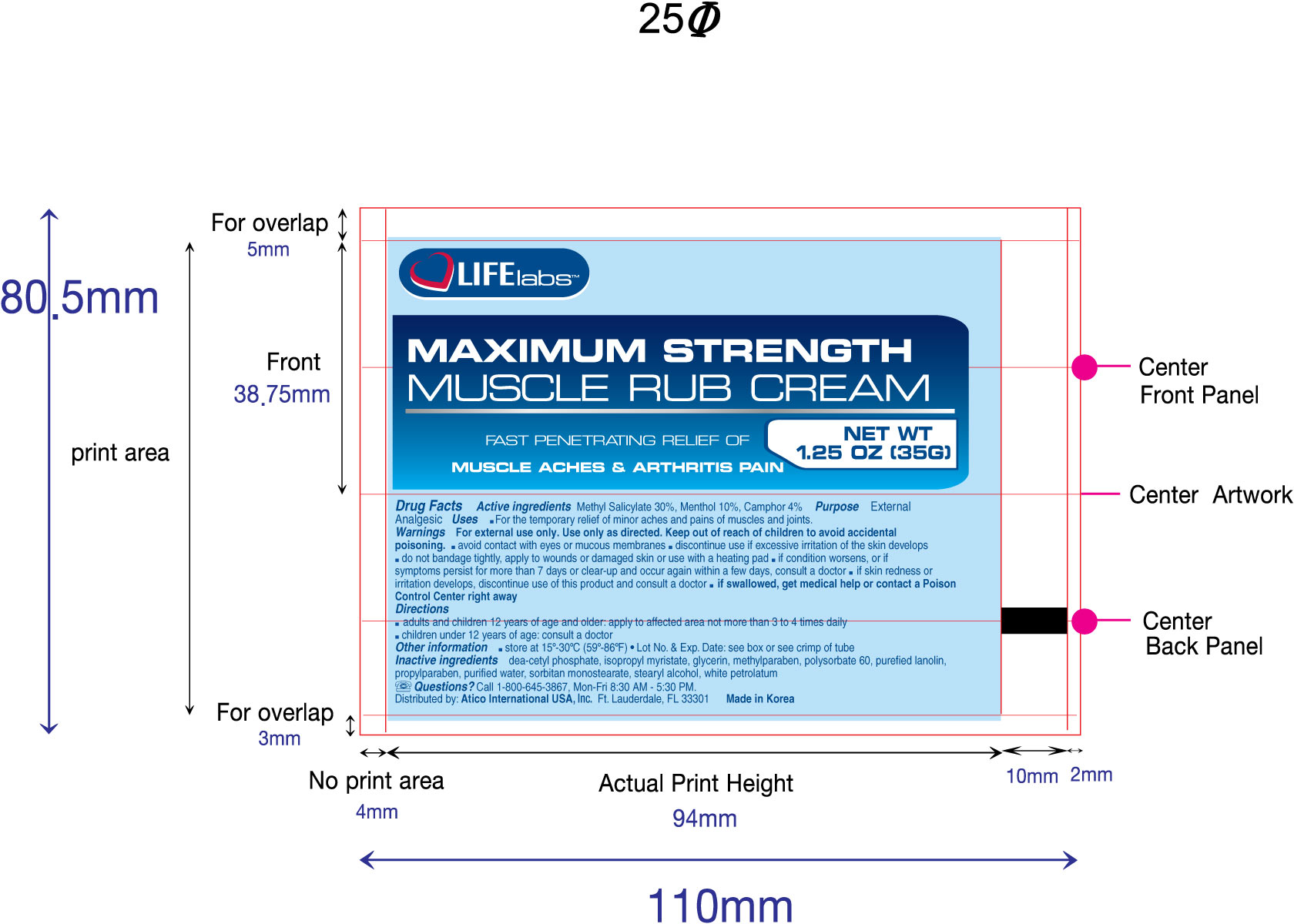 DRUG LABEL: Muscle Rub
NDC: 51852-105 | Form: CREAM
Manufacturer: LIFElabs, a Division of Atico International USA, INC.
Category: otc | Type: HUMAN OTC DRUG LABEL
Date: 20100817

ACTIVE INGREDIENTS: Methyl Salicylate 300 mg/1 g; Menthol 100 mg/1 g; Camphor (Synthetic) 40 mg/1 g
INACTIVE INGREDIENTS: Diethanolamine Cetyl Phosphate; Isopropyl Myristate; Glycerin; Methylparaben; Polysorbate 60; Lanolin; Propylparaben; Water; Sorbitan Monostearate; Stearyl Alcohol; Petrolatum

LIFElabs, a Division of Atico International USA, INC.

Muscle Rub (Maximum Strength)

Active Ingredients

Methyl Salicylate - 30%, Menthol - 10%, Camphor - 4%

Purpose

External Analgesic

Warnings

For external use only. Use only as directed. Keep out of reach of children to avoid accidental poisoning.

- avoid contact with eyes or mucous membranes.
- discontinue use if excessive irritation of the skin develops.
- do not bandage tightly, apply to wounds, or damaged skin, or use with a heating pad
- if condition worsens, or if symptoms persist for more than 7 days or clear-up and occur again within a few days, consult a doctor
- if skin redness or irritation develops, discontinue use of this product and consult a doctor.
- if swallowed, get medical help or contact a Poison Control Center right away.

Uses

- For the temporary relief of minor aches and pains of muscles and joints.

Other Information

- Store at controlled room temperature 15o to 30o C (59o to 86oF)
- Lot No. and Exp. Date: see box or see crimp of tube

Directions

- Adults and children 12 years of age and older: apply to the affected area not more than 3 to 4 times daily
- Children under 12 years of age: consult a doctor.

Inactive Ingredients

dea-cetyl phosphate, isopropyl myristate, glycerin, methylparaben, polysorbate 60, purefied lanolin, propylparaben, purified water, sorbitan monostearate, stearyl alcohol, white petrolatum

QUESTIONS

Questions? Call 1-800-645-3867, Mon-Fri 8:30 AM - 5:30 PM.

Keep out of reach of children to avoid accidental poisoning.